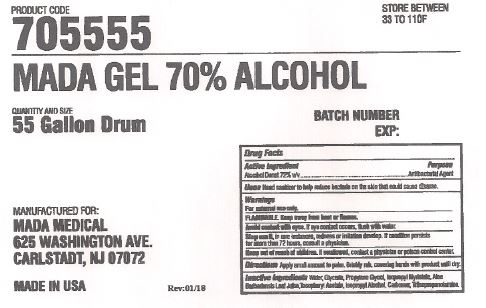 DRUG LABEL: Mada 70% Alcohol
NDC: 11928-005 | Form: GEL
Manufacturer: Mada Medical Products, Inc.
Category: otc | Type: HUMAN OTC DRUG LABEL
Date: 20241120

ACTIVE INGREDIENTS: ALCOHOL 72 L/100 L
INACTIVE INGREDIENTS: WATER; GLYCERIN; PROPYLENE GLYCOL; ISOPROPYL MYRISTATE; ALOE VERA LEAF; .ALPHA.-TOCOPHEROL ACETATE; ISOPROPYL ALCOHOL; CARBOXYPOLYMETHYLENE; TRIISOPROPANOLAMINE

11928-005 Mada 70% Alcohol

Active ingredient

Alcohol Denat. 72% v/v

Purpose

Antibacterial Agent

Uses

Hand sanitizer to help reduce bacteria on the skin that could cause disease.

Warnings

For external use only.

FLAMMABLE Keep away from heat or flame.

WHEN USING

Avoid contact with eyes.

If eye contact occurs, flush with water.

Stop use if, in rare instances, redness or irritation develop.

If condition persists for more than 72 hours, consult a physician.

Keep out of reach of children.

If swallowed, contact a physician or poison control center.

Directions

Apply a small amount to palm.

Briefly rub, covering hands with product until dry.

Inactive ingredients

Water, Glycerin, Propylene Glycol, Isopropyl Myristate, Aloe Barbadensis Leaf Juice, Tocopheryl Acetate, Isopropyl Alcohol, Carbomer, Triisopropanolamine

PACKAGE LABEL

PRODUCT CODE

705555

STORE BETWEEN

33 TO 110F

MADA GEL 70% ALCOHOL

QUANTITY AND SIZE

55 Gallon Drum

BATCH NUMBER

EXP:

MANUFACTURED FOR:

MADA MEDICAL

625 WASHINGTON AVE.

CARLSTADT. NJ 07072

MADE IN USA

Rev:01/18